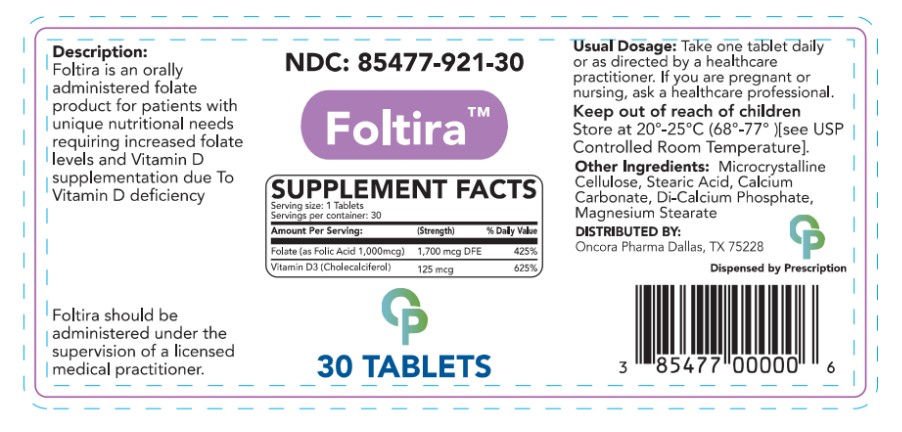 DRUG LABEL: Foltira
NDC: 85477-921 | Form: TABLET
Manufacturer: Oncora Pharma, LLC
Category: prescription | Type: HUMAN PRESCRIPTION DRUG LABEL
Date: 20251215

ACTIVE INGREDIENTS: FOLATE SODIUM 1.7 mg/1 1; VITAMIN D 0.125 mg/1 1
INACTIVE INGREDIENTS: CALCIUM CARBONATE; STEARIC ACID; CELLULOSE, MICROCRYSTALLINE; CALCIUM PHOSPHATE, DIBASIC, DIHYDRATE; MAGNESIUM STEARATE

DESCRIPTION

Foltira is an orally administered prescription folate product.

INDICATIONS AND USAGE

Foltira is for patients with unique nutritional needs requiring increased folate levels and Vitamin D supplementation due to Vitamin D deficiency.

PRECAUTIONS

Foltira should be administered under the supervision of a licensed medical practitioner.

Keep out of reach of children.

DOSAGE AND ADMINISTRATION

Take one tablet daily or as directed by a licensed medical practitioner. If you are pregnant or nursing ask a healthcare professional.

OTHER SAFETY INFORMATION

Store at 20ºC - 25ºC (68º-77ºF) [See USP Controlled Room Temperature.]

HOW SUPPLIED

NDC 85477-921-30

Distributed by:

Oncora Pharma

Dallas, Texas 75228